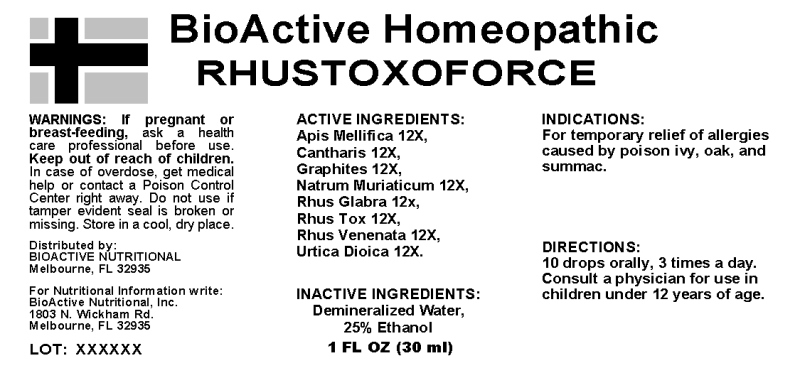 DRUG LABEL: Rhustoxoforce
NDC: 43857-0206 | Form: LIQUID
Manufacturer: BioActive Nutritional, Inc.
Category: homeopathic | Type: HUMAN OTC DRUG LABEL
Date: 20241018

ACTIVE INGREDIENTS: APIS MELLIFERA 12 [hp_X]/1 mL; LYTTA VESICATORIA 12 [hp_X]/1 mL; GRAPHITE 12 [hp_X]/1 mL; SODIUM CHLORIDE 12 [hp_X]/1 mL; RHUS GLABRA TOP 12 [hp_X]/1 mL; TOXICODENDRON PUBESCENS LEAF 12 [hp_X]/1 mL; TOXICODENDRON VERNIX LEAFY TWIG 12 [hp_X]/1 mL; URTICA DIOICA WHOLE 12 [hp_X]/1 mL
INACTIVE INGREDIENTS: WATER; ALCOHOL

DRUG FACTS:

ACTIVE INGREDIENTS:

Apis Mellifica 12X, Cantharis 12X, Graphites 12X, Natrum Muriaticum 12X, Rhus Glabra 12X, Rhus Toxidodendron 12X, Rhus Venenata 12X, Urtica Dioica 12X

INDICATIONS:

For temporary relief of allergies caused by poison ivy, oak, and summac.

WARNINGS:

If pregnant or breast-feeding, ask a health care professional befure use.

Keep out of reach of children. In case of overdose, get medical help or contact a Poison Control Center right away.

Do not use if tamper evident seal is broken or missing.

Store in a cool, dry place.

DIRECTIONS:

10 drops orally, 3 times a day. Consult a physician for use in children under 12 years of age.

INACTIVE INGREDIENTS:

Demineralized Water, 25% Ethanol

Keep out of reach of children. In case of overdose, get medical help or contact a Poison Control Center right away.

INDICATIONS:

For temporary relief of allergies caused by poison ivy, oak, and summac.

QUESTIONS:

Distributed by:

BIOACTIVE NUTRITIONAL

Melbourne, FL 32935

For Nutritional Information write:

BioActive Nutritional, Inc.

1803 N. Wickham Rd.

Melbourne, Fl 32935

PACKAGE LABEL DISPLAY:

BioActie Homeopathic

RHUSTOXOFORCE

1 FL OZ (30 mL)